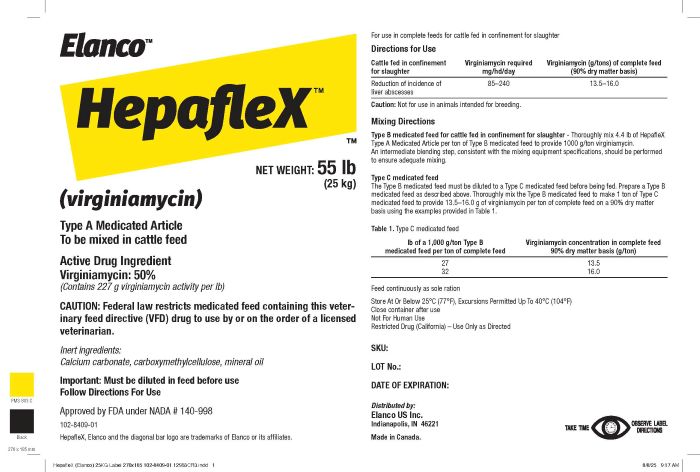 DRUG LABEL: HepafleX
NDC: 58198-1504 | Form: POWDER
Manufacturer: ELANCO US. INC
Category: animal | Type: VFD TYPE A MEDICATED ARTICLE ANIMAL DRUG LABEL
Date: 20250926

ACTIVE INGREDIENTS: VIRGINIAMYCIN 227 g/0.45 kg
INACTIVE INGREDIENTS: CALCIUM CARBONATE; MINERAL OIL; CARBOXYMETHYLCELLULOSE SODIUM, UNSPECIFIED FORM; SOYBEAN OIL; RICE BRAN

HepafleXTM
(virginiamycin)
Type A Medicated Article

WARNINGS AND PRECAUTIONS

To be mixed in cattle feed

Active Drug Ingredient

Virginiamycin: 50%

(Contains 227 g virginiamycin activity per lb)

CAUTION:

CAUTION: Federal law restricts medicated feed containing this veterinary feed directive (VFD) drug to use by or on the order of a licensed veterinarian.

Inert ingredients:

Calcium carbonate, carboxymethylcellulose, mineral oil

Important: Must be diluted in feed before use

Follow Directions For Use

Approved by FDA under NADA # 140-998

102-8409-1

HepafleX, Elanco and the diagonal bar logo are trademarks of Elanco or its affiliates.

NET WEIGHT: 55 lb (25kg)

Distributed by:

Elanco US Inc.

Indianapolis, IN 46221

Made in Canada

For use in complete feeds for cattle fed in confinement for slaughter Directions for Use

Cattle fed in confinement for slaughter | Virginiamycin required mg/hd/day | Virginiamycin (g/tons) of complete feed (90% dry matter basis)
Reduction of incidence of liver abscesses | 85-240 | 13.5-16.0
Caution: Not for use in animals intended for breeding.

Mixing Directions

Type B medicated feed for cattle fed in confinement for slaughter - Thoroughly mix 4.4 lb of HepafleX Type A Medicated Article per ton of Type B medicated feed to provide 1000 g/ton virginiamycin.
An intermediate blending step, consistent with the mixing equipment specifications, should be performed to ensure adequate mixing.

Type C medicated feed
The Type B medicated feed must be diluted to a Type C medicated feed before being fed. Prepare a Type B medicated feed as described above. Thoroughly mix the Type B medicated feed to make 1 ton of Type C medicated feed to provide 13.5–16.0g of virginiamycin per ton of complete feed on a 90% dry matter basis using the examples provided in Table 1.

Table 1. Type C medicated feed

lb of a 1,000 g/ton Type B medicated feed per ton of complete feed | Virginiamycin concentration in complete feed 90% dry matter basis (g/ton)
27 | 13.5
32 | 16.0

Feed continuously as sole ration

STORAGE AND HANDLING

Store At Or Below 25°C (77°F), Excursions Permitted Up To 40°C (104°F)
Close container after use

SKU:
LOT No.:
DATE OF EXPIRATION:
Distributed by:
Elanco US Inc.
Indianapolis, IN 46221
Made in Canada.

INDICATIONS AND USAGE

Not For Human Use
Restricted Drug (California) – Use Only as Directed

Hepaflex

Label